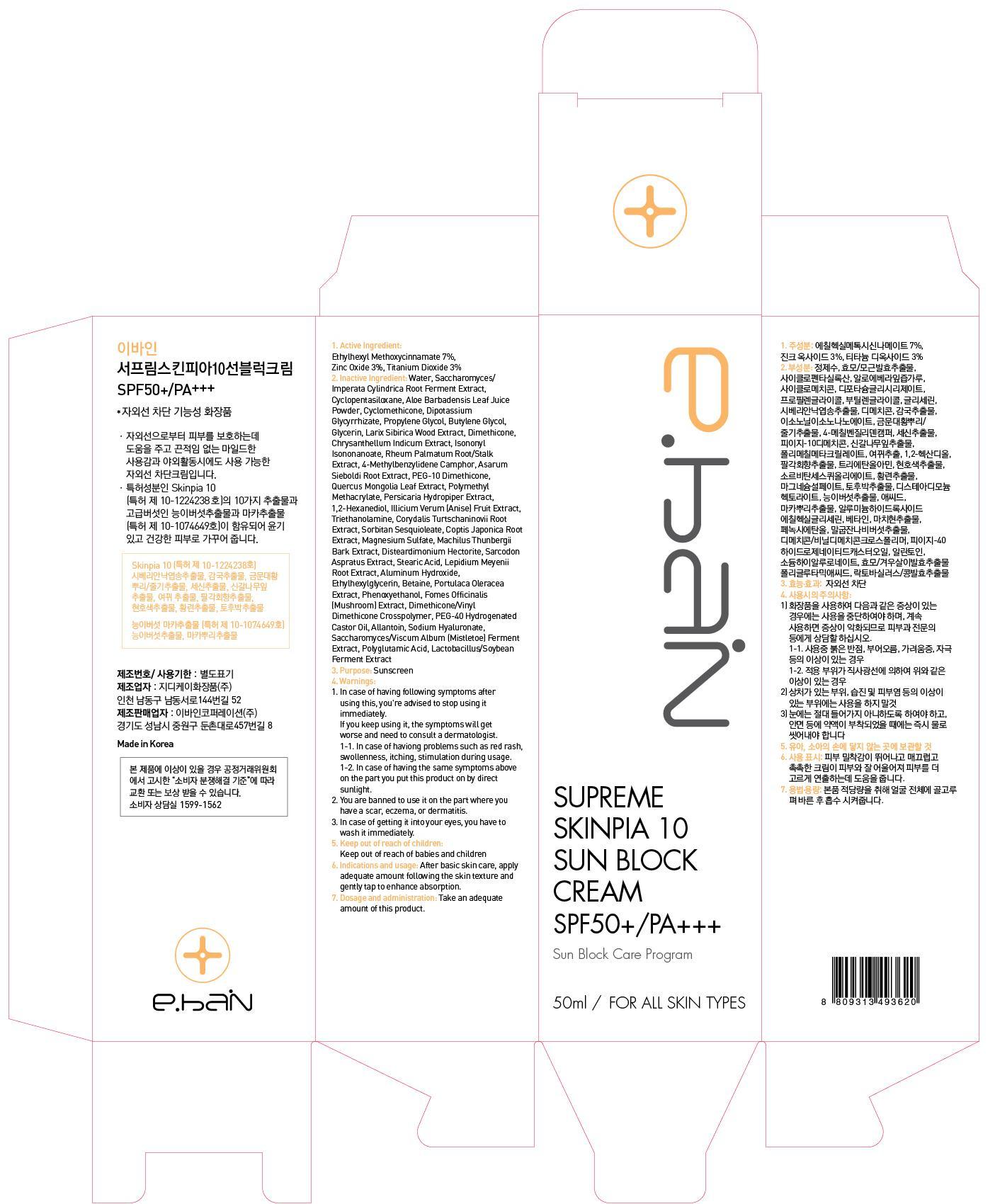 DRUG LABEL: SUPREME SKINPIA 10 SUN BLOCK
NDC: 62242-010 | Form: CREAM
Manufacturer: EBAIN Corporation Co., Ltd.
Category: otc | Type: HUMAN OTC DRUG LABEL
Date: 20140304

ACTIVE INGREDIENTS: Octinoxate 3.5 mg/50 mL; Zinc Oxide 1.5 mg/50 mL; Titanium Dioxide 1.5 mg/50 mL
INACTIVE INGREDIENTS: Water; Propylene Glycol

ACTIVE INGREDIENT

Active Ingredients: Ethylhexyl Methoxycinnamate 7%, Zinc Oxide 3%, Titanium Dioxide 3%

INACTIVE INGREDIENT

Inactive Ingredients:
Water, Cyclopentasiloxane, Cyclomethicone, Propylene Glycol, Glycerin, Dimethicone, Isononyl Isononanoate, 4-Methylbenzylidene Camphor, PEG-10 Dimethicone, Polymethyl Methacrylate, 1,2-Hexanediol, Triethanolamine, Sorbitan Sesquioleate, Magnesium Sulfate,
Disteardimonium Hectorite, Stearic Acid, Aluminum Hydroxide, Betaine, Phenoxyethanol, Dimethicone/Vinyl Dimethicone Crosspolymer, Allantoin, Saccharomyces/Viscum Album (Mistletoe) Ferment Extract, Lactobacillus/Soybean Ferment Extract, Saccharomyces/Imperata Cylindrica Root Ferment Extract, Aloe Barbadensis Leaf Juice Powder, Dipotassium Glycyrrhizate, Butylene Glycol, Larix Sibirica Wood Extract, Chrysanthellum Indicum Extract, Rheum Palmatum Root/Stalk Extract, Asarum Sieboldi Root Extract, Quercus Mongolia Leaf Extract , Persicaria Hydropiper Extract, Illicium Verum (Anise) Fruit Extract, Corydalis Turtschaninovii Root Extract, Coptis Japonica Root Extract, Machilus Thunbergii Bark Extract, Sarcodon Aspratus Extract, Lepidium Meyenii Root Extract, Ethylhexylglycerin, Portulaca Oleracea Extract, Fomes Officinalis (Mushroom) Extract, PEG-40 Hydrogenated Castor Oil, Sodium Hyaluronate, Polyglutamic Acid

PURPOSE

Purpose: Sunscreen

WARNINGS

1. In case of having following symptoms after using this, you're advised to stop using it immediately.
If you keep using it, the symptoms will get worse and need to consult a dermatologist.
- In case of haviong problems such as red rash, swollenness, itching, stimulation during usage.
- In case of having the same symptoms above on the part you put this product on by direct sunlight.
2. You are banned to use it on the part where you have a scar, eczema, or dermatitis.
3. In case of getting it into your eyes, you have to wash it immediately.

Keep out of reach of children: Keep out of reach of babies and children

Indications and usage: After basic skin care, apply adequate amount following the skin texture and gently tap to enhance absorption.

Dosage and administration: Take an adequate amount of this product.